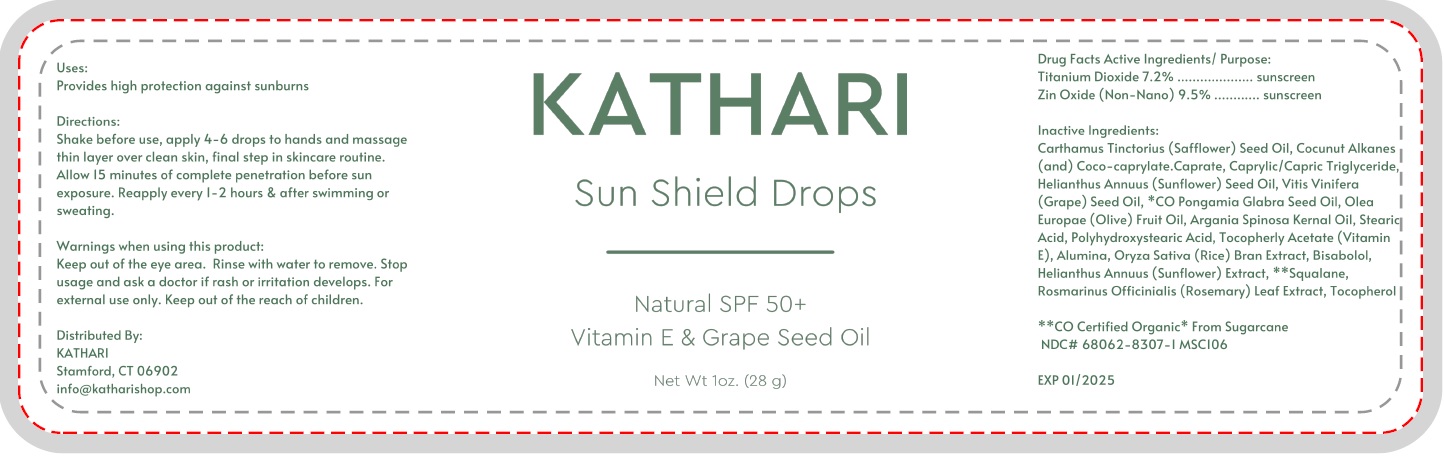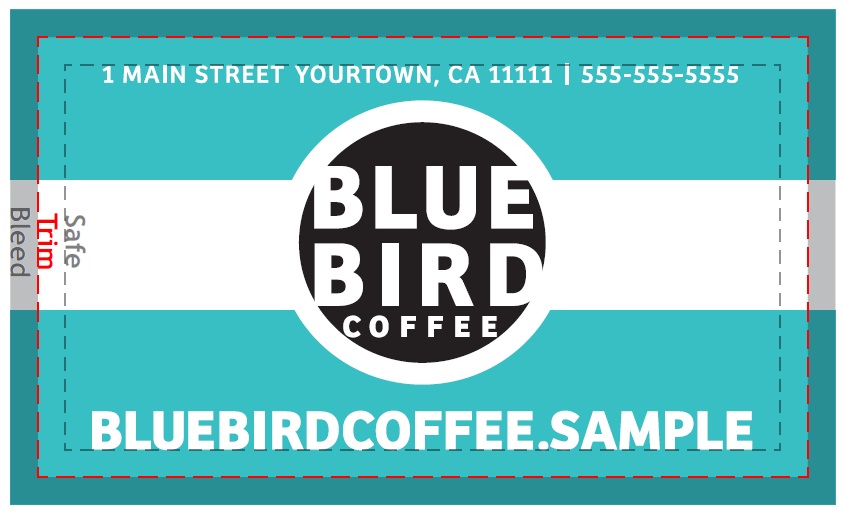 DRUG LABEL: Kathari Sun Shield Drops Natural SPF 50
NDC: 82710-000 | Form: OIL
Manufacturer: Kathari LLC
Category: otc | Type: HUMAN OTC DRUG LABEL
Date: 20220510

ACTIVE INGREDIENTS: TITANIUM DIOXIDE 72 mg/1 g; ZINC OXIDE 95 mg/1 g
INACTIVE INGREDIENTS: SAFFLOWER OIL; COCONUT ALKANES; COCO-CAPRYLATE; MEDIUM-CHAIN TRIGLYCERIDES; SUNFLOWER OIL; GRAPE SEED OIL; KARUM SEED OIL; OLIVE OIL; ARGAN OIL; STEARIC ACID; .ALPHA.-TOCOPHEROL ACETATE; ALUMINUM OXIDE; RICE BRAN; LEVOMENOL; HELIANTHUS ANNUUS FLOWERING TOP; SQUALANE; ROSEMARY; TOCOPHEROL

Kathari Sun Shield Drops Natural SPF 50

Active Ingredients

Titanium Dioxide 7.2%

Zin Oxide (Non-Nano) 9.5%

Purpose:

sunscreen

Inactive Ingredients:

Carthamus Tinctorius (Safflower) Seed Oil, Cocunut Alkanes (and) Coco-caprylate. Caprate, Caprylic/Capric Triglyceride, Helianthus Annuus (Sunflower) Seed Oil, Vitis Vinifera (Grape) Seed Oil, *CO Pongamia Glabra Seed Oil, Olea Europae (Olive) Fruit Oil, Argania Spinosa Kernal Oil, Steario Acid, Polyhydroxystearic Acid, Tocopheryl Acetate (Vitamin E), Alumina, Oryza Sativa (Rice) Bran Extract, Bisabolol, Helianthus Annuus (Sunflower) Extract, **Squalane, Rosmarinus Officinialis (Rosemary) Leaf Extract, Tocopherol

Uses:

Provides high protection against sunburns

Directions:

Shake before use, apply 4-6 drops to hands and massage thin layer over clean skin, final step in skincare routine. Allow 15 minutes of complete penetration before sun exposure. Reapply every 1-2 hours & after swimming or sweating.

Warnings

when using this product

Keep out of the eye area. Rinse with water to remove.

Stop usage and ask a doctor

if rash or irritation develops. For external use only.